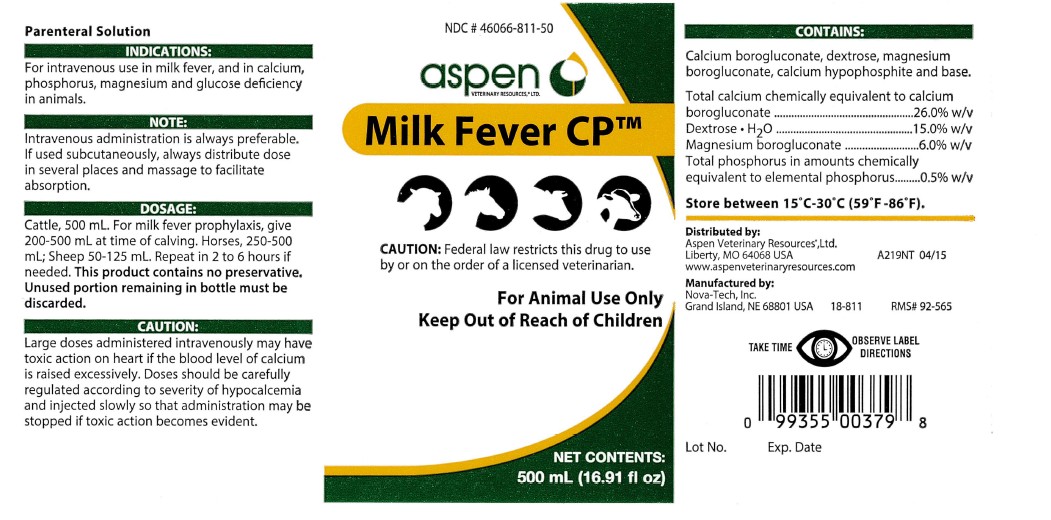 DRUG LABEL: Milk Fever CP
NDC: 46066-811 | Form: INJECTION, SOLUTION
Manufacturer: Aspen Veterinary
Category: animal | Type: PRESCRIPTION ANIMAL DRUG LABEL
Date: 20250909

ACTIVE INGREDIENTS: Calcium Borogluconate 130 g/500 mL; Dextrose Monohydrate 75 g/500 mL; Magnesium Gluconate 30 g/500 mL; Phosphorus 2.5 g/500 mL

Milk Fever CP

CAUTION:

Federal law restricts this drug to use
by or on the order of a licensed veterinarian.

GENERAL PRECAUTIONS

For Animal Use Only
Keep Out of Reach of Children

INFORMATION FOR OWNERS/CAREGIVERS

NET CONTENTS:
500 mL (16.91 fl oz)

INFORMATION FOR OWNERS/CAREGIVERS

Parenteral Solution

INDICATIONS:

For intravenous use in milk fever, and in calcium,
phosphorus, magnesium and glucose deficiency
in animals.

NOTE:

Intravenous administration is always preferable.
If used subcutaneously, always distribute dose
in several places and massage to facilitate
absorption.

DOSAGE:

Cattle, 500 mL. For milk fever prophylaxis, give
200-500 mL at time of calving. Horses, 250-500
mL; Sheep 50-125 mL. Repeat in 2 to 6 hours if
needed. This product contains no preservative.
Unused portion remaining in bottle must be
discarded.

CAUTION:

Large doses administered intravenously may have
toxic action on heart if the blood level of calcium
is raised excessively. Doses should be carefully
regulated according to severity of hypocalcemia
and injected slowly so that administration may be
stopped if toxic action becomes evident.

CONTAINS:

Calcium borogluconate, dextrose, magnesium
borogluconate, calcium hypophosphite and base.
Total calcium chemically equivalent to calcium
borogluconate...................................26.0% w/v
Dextrose . H2O..................................15.0% w/v
Magnesium borogluconate..................6.0% w/v
Total phosphorus in amounts chemically
equivalent to elemental phosphorus.....0.5% w/v

STORAGE AND HANDLING

Store between 15 degrees C-30 degrees C (59degrees F-86 degrees F).

GENERAL PRECAUTIONS

TAKE TIME OBSERVE LABEL DIRECTIONS

INFORMATION FOR OWNERS/CAREGIVERS

Distributed by:
Aspen Veterinary ResourcesR, Ltd.
Liberty, MO 64068 USA
www.aspenveterinaryresources.com

Manufactured by:
Nova-Tech, Inc.
Grand Island, NE 68801 USA 18-811 RMS# 92-565

Lot No. Exp. Date